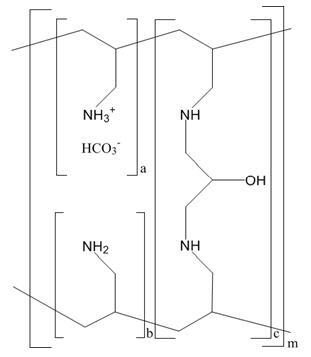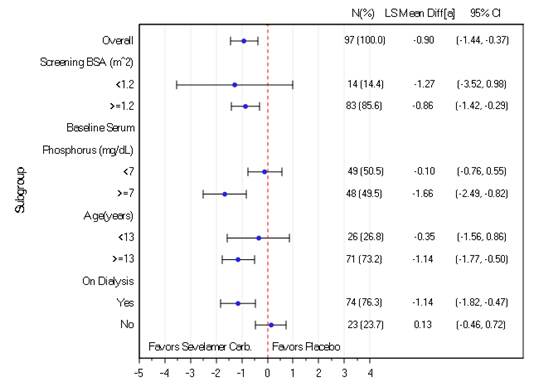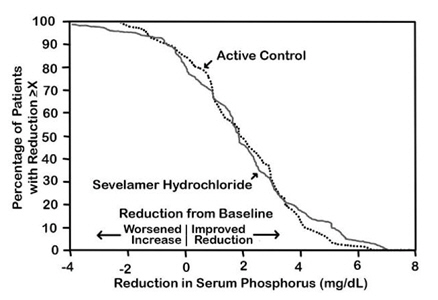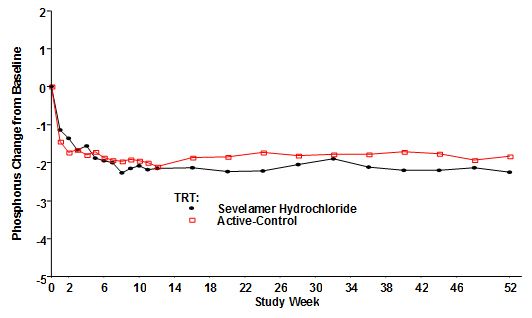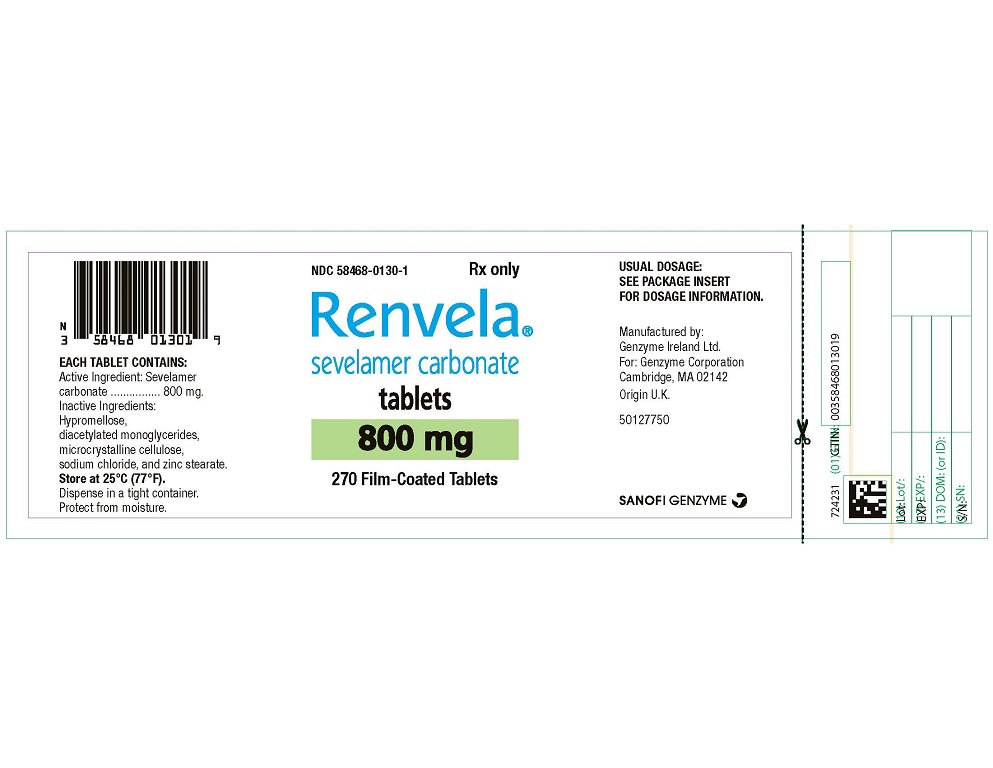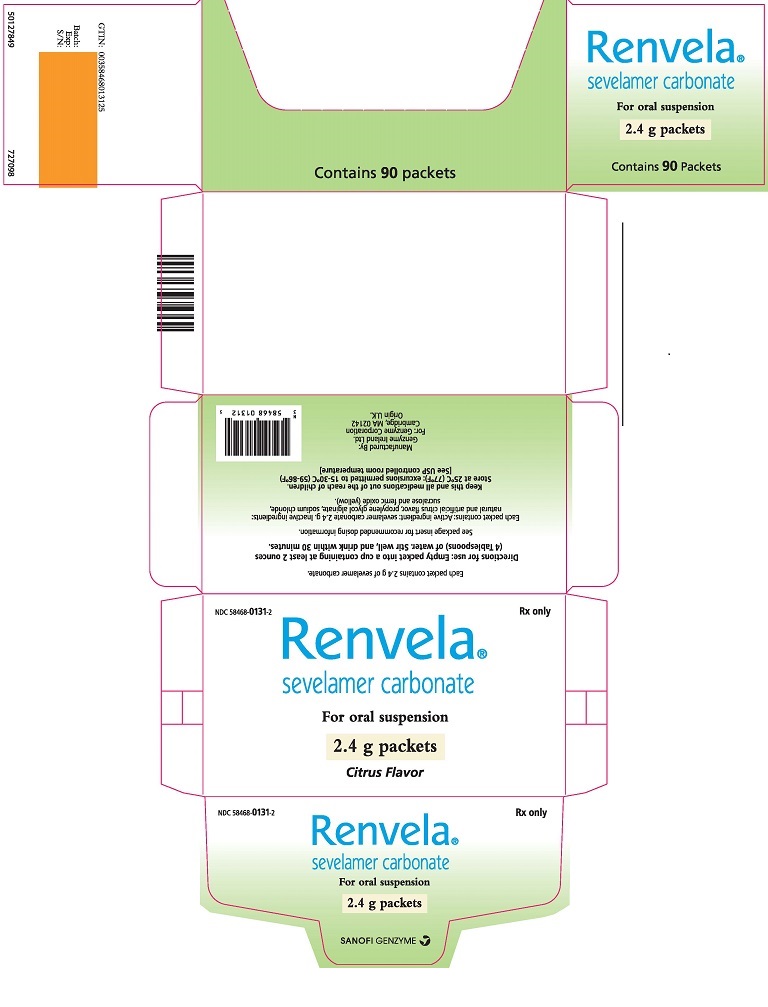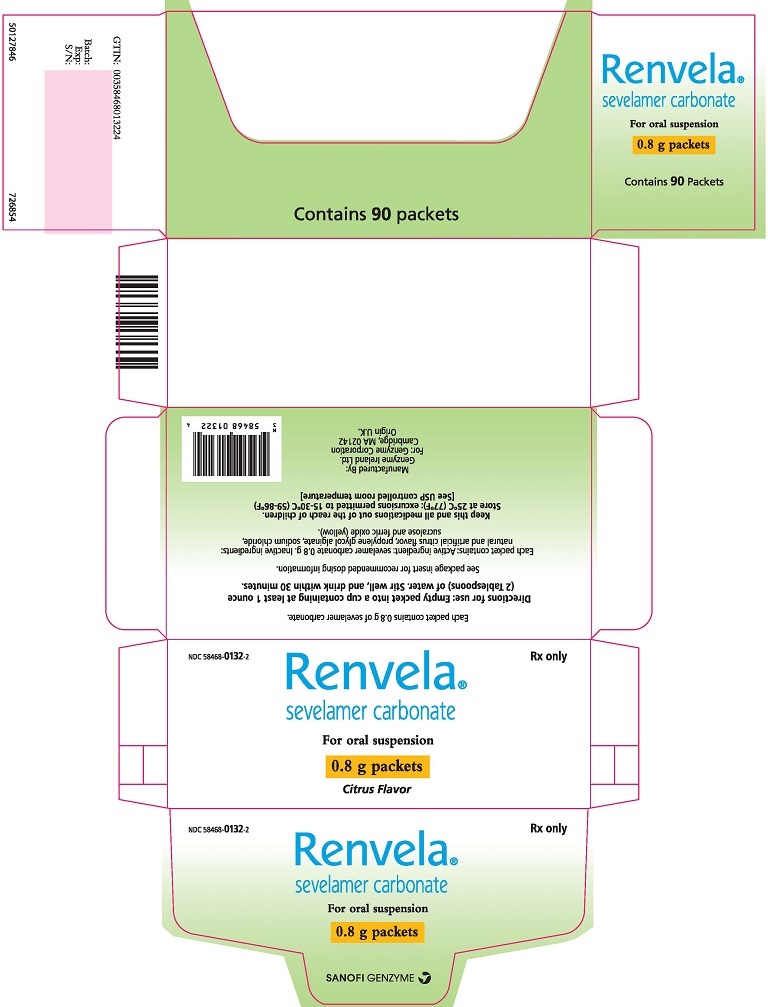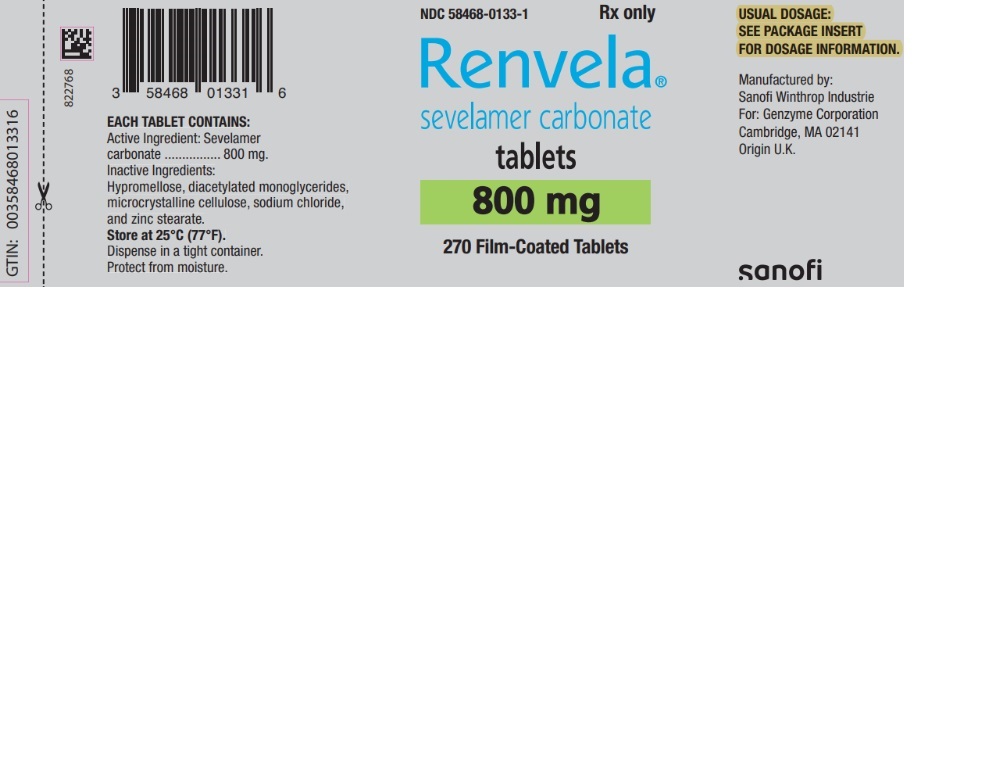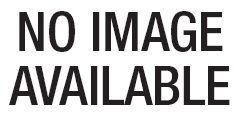 DRUG LABEL: Renvela
NDC: 58468-0131 | Form: POWDER, FOR SUSPENSION
Manufacturer: Genzyme Corporation
Category: prescription | Type: HUMAN PRESCRIPTION DRUG LABEL
Date: 20251125

ACTIVE INGREDIENTS: SEVELAMER CARBONATE 2400 mg/1 1
INACTIVE INGREDIENTS: PROPYLENE GLYCOL ALGINATE; SODIUM CHLORIDE; SUCRALOSE; FERRIC OXIDE YELLOW

HIGHLIGHTS OF PRESCRIBING INFORMATION

These highlights do not include all the information needed to use RENVELA safely and effectively. See full prescribing information for RENVELA.
RENVELA (sevelamer carbonate) tablets, for oral use
RENVELA (sevelamer carbonate) powder, for oral suspension
Initial U.S. Approval: 2000

1 INDICATIONS AND USAGE

Renvela®is a phosphate binder indicated for the control of serum phosphorus in adults and children 6 years of age and older with chronic kidney disease on dialysis. (1)

2 DOSAGE AND ADMINISTRATION

- Starting dose of Renvela is 0.8 or 1.6 grams administered orally three times per day with meals based on serum phosphorus levels for adult patients and based on body surface area (BSA) category for pediatric patients. (2.1)
- Titrate by 0.8 g per meal in two-week intervals for adult patients as needed to obtain serum phosphorus target. (2.1)
- Titrate based on BSA category for pediatric patients in two-week intervals for 6 weeks and then every 4 weeks as needed to obtain serum phosphorus target. (2.1)

3 DOSAGE FORMS AND STRENGTHS

- Tablets: 800 mg (3)
- Powder: 0.8 g and 2.4 g packets (3)

4 CONTRAINDICATIONS

- Bowel obstruction. (4)
- Known hypersensitivity to sevelamer carbonate, sevelamer hydrochloride, or to any of the excipients. (4)

5 WARNINGS AND PRECAUTIONS

- Serious cases of dysphagia, bowel obstruction, bleeding gastrointestinal ulcers, colitis, ulceration, necrosis, and perforation have been associated with sevelamer use, some requiring hospitalization and surgery. (5.1)

6 ADVERSE REACTIONS

- Most of the safety experience is with sevelamer carbonate tablets and sevelamer hydrochloride. In long-term studies with sevelamer hydrochloride, which contains the same active moiety as sevelamer carbonate, the most common adverse events included: vomiting (22%), nausea (20%), diarrhea (19%), dyspepsia (16%), abdominal pain (9%), flatulence (8%), and constipation (8%). (6.1)

To report SUSPECTED ADVERSE REACTIONS, contact Genzyme Corporation at 1-800-847-0069 or FDA at 1-800-FDA-1088 or www.fda.gov/medwatch.

7 DRUG INTERACTIONS

- For oral medication where a reduction in the bioavailability of that medication would have a clinically significant effect on its safety or efficacy, consider separation of the timing of administration and/or monitor clinical responses or blood levels of the concomitant medication. (7)
- Sevelamer did not alter the pharmacokinetics of digoxin, enalapril, iron, metoprolol and warfarin. (7)
- Sevelamer has demonstrated interaction with ciprofloxacin, mycophenolate mofetil, and therefore, these drugs should be dosed separately from Renvela. (7)

FULL PRESCRIBING INFORMATION

1 INDICATIONS AND USAGE

Renvela®(sevelamer carbonate) is indicated for the control of serum phosphorus in adults and children 6 years of age and older with chronic kidney disease (CKD) on dialysis.

2 DOSAGE AND ADMINISTRATION

2.1 General Dosing Information

Starting Dose for Adult Patients Not Taking a Phosphate Binder.The recommended starting dose of Renvela is 0.8 to 1.6 g taken orally with meals based on serum phosphorus level. Table 1 provides recommended starting doses of Renvela for adult patients not taking a phosphate binder.

Table 1: Starting Dose for Adult Dialysis Patients Not Taking a Phosphate Binder
Serum Phosphorus | Renvela
>5.5 and <7.5 mg/dL | 0.8 g three times daily with meals
≥7.5 mg/dL | 1.6 g three times daily with meals

Dose Titration for Adult Patients Taking Renvela. Titrate the Renvela dose by 0.8 g three times per day with meals at two-week intervals as necessary to achieve target serum phosphorus levels. Based on clinical studies, the average prescribed adult daily dose of sevelamer carbonate is approximately 7.2 g per day. The highest daily adult dose of sevelamer carbonate studied was 14 grams in CKD patients on dialysis.

Starting Dose for Pediatric Patients Not Taking a Phosphate Binder.The recommended starting dose for pediatric patients 6 years of age and older is 0.8 to 1.6 g taken three times per day with meals based on the patient's body surface area (BSA) category; see Table 2.

Table 2: Recommended Starting Dosage and Titration Increment Based on Pediatric Patient's Body Surface Area (m^2)
BSA (m^2) | Starting Dose Per Meal/Snack | Titration Increases/Decreases Per Dose
≥0.75 to <1.2 | 0.8 g | Titrate by 0.4 g
≥1.2 | 1.6 g | Titrate by 0.8 g

Dose Titration for Pediatric Patients Taking Renvela.Titrate the Renvela dose as needed to achieve target levels at two-week intervals based on BSA category, as shown in Table 2.

Switching from Sevelamer Hydrochloride Tablets.For adult patients switching from sevelamer hydrochloride tablets to sevelamer carbonate tablets or powder, use the same dose in grams.

Switching between Sevelamer Carbonate Tablets and Powder.Use the same dose in grams.

Switching from Calcium Acetate. Table 3 gives recommended starting doses of Renvela based on a patient's current calcium acetate dose.

Table 3: Starting Dose for Dialysis Patients Switching from Calcium Acetate to Renvela
Calcium Acetate 667 mg (Tablets per meal) | Renvela
1 tablet | 0.8 g
2 tablets | 1.6 g
3 tablets | 2.4 g

2.2 Sevelamer Carbonate Powder Preparation Instructions

Sevelamer carbonate powder is available in 0.8 or 2.4 g packets. For dose increments of 0.4 g, use one half of a 0.8 g packet. Place the sevelamer carbonate powder in a cup and suspend in the amount of water described in Table 4.

Table 4: Sevelamer Carbonate Powder Preparation Instructions
Amount of Renvela Powder | Minimum Amount of Water for Dose Preparation (either ounces, mL, or tablespoon)
Amount of Renvela Powder | Ounces | mL | Tablespoons
0.4 g | 1 | 30 | 2
0.8 g | 1 | 30 | 2
2.4 g | 2 | 60 | 4

Instruct patients to stir the mixture vigorously (it does not dissolve), resuspend, if necessary, right before administration, and drink the entire preparation within 30 minutes.

As an alternative to water, the entire contents of the packet may be pre-mixed with a small amount of food or beverage and consumed immediately (within 30 minutes) as part of the meal. Do not heat Renvela powder (e.g., microwave) or add to heated foods or liquids.

3 DOSAGE FORMS AND STRENGTHS

Tablets: 800 mg white oval, film-coated, compressed tablets, engraved with RV800 on one side

Powder: 0.8 g and 2.4 g pale-yellow powder packaged in an opaque, foil-lined, heat-sealed packets

4 CONTRAINDICATIONS

Renvela is contraindicated in patients with bowel obstruction.

Renvela is contraindicated in patients with known hypersensitivity to sevelamer carbonate, sevelamer hydrochloride, or to any of the excipients.

5 WARNINGS AND PRECAUTIONS

5.1 Gastrointestinal Adverse Events

Patients with dysphagia, swallowing disorders, severe gastrointestinal (GI) motility disorders, including severe constipation, or major GI tract surgery were not included in the Renvela clinical studies.

Cases of dysphagia and esophageal tablet retention have been reported in association with use of the tablet formulation of sevelamer, some requiring hospitalization and intervention. Consider using sevelamer suspension in patients with a history of swallowing disorders.

Cases of bowel obstruction, bleeding gastrointestinal ulcers, colitis, ulceration, necrosis, and perforation have also been reported with sevelamer use [see Adverse Reactions (6.2)] . Inflammatory disorders may resolve upon Renvela discontinuation. Treatment with Renvela should be re-evaluated in patients who develop severe gastrointestinal symptoms.

5.2 Reductions in Vitamins D, E, K (clotting factors) and Folic Acid Levels

In preclinical studies in rats and dogs, sevelamer hydrochloride, which contains the same active moiety as sevelamer carbonate, reduced vitamins D, E, and K (coagulation parameters) and folic acid levels at doses of 6–10 times the recommended human dose. In short-term clinical trials, there was no evidence of reduction in serum levels of vitamins. However, in a one-year clinical trial, 25-hydroxyvitamin D (normal range 10 to 55 ng/mL) fell from 39 ± 22 ng/mL to 34 ± 22 ng/mL (p<0.01) with sevelamer hydrochloride treatment. Most (approximately 75%) patients in sevelamer hydrochloride clinical trials were receiving vitamin supplements.

6 ADVERSE REACTIONS

6.1 Clinical Trials Experience

Because clinical trials are conducted under widely varying conditions, adverse reaction rates observed in the clinical trials of a drug cannot be directly compared to rates in the clinical trials of another drug and may not reflect the rates observed in practice.

There are limited clinical trial data on the safety of Renvela. However, because it contains the same active ingredient as the hydrochloride salt, the adverse event profiles of the two salts are expected to be similar. In a cross-over study in hemodialysis patients with treatment durations of eight weeks each and no washout, and another cross-over study in hemodialysis patients with treatment durations of four weeks each and no washout between treatment periods, the adverse reactions on sevelamer carbonate powder were similar to those reported for sevelamer hydrochloride.

In a parallel design study of sevelamer hydrochloride with treatment duration of 52 weeks, adverse reactions reported for sevelamer hydrochloride (n=99) were similar to those reported for the active-comparator group (n=101). Overall adverse reactions among those treated with sevelamer hydrochloride occurring in >5% of patients included: vomiting (22%), nausea (20%), diarrhea (19%), dyspepsia (16%), abdominal pain (9%), flatulence (8%), and constipation (8%). A total of 27 patients treated with sevelamer and 10 patients treated with comparator withdrew from the study due to adverse reactions.

Based on studies of 8–52 weeks, the most common reason for withdrawal from sevelamer hydrochloride was gastrointestinal adverse reactions (3%–16%).

In 143 peritoneal dialysis patients studied for 12 weeks using sevelamer hydrochloride, most common adverse reactions were similar to adverse reactions observed in hemodialysis patients. The most frequently occurring treatment emergent serious adverse reaction was peritonitis (8 reactions in 8 patients [8%] in the sevelamer group and 2 reactions in 2 patients [4%] on active control). Thirteen patients (14%) in the sevelamer group and 9 patients (20%) in the active-control group discontinued, mostly for gastrointestinal adverse reactions.

6.2 Postmarketing Experience

Because these reactions are reported voluntarily from a population of uncertain size, it is not always possible to reliably estimate their frequency or to establish a causal relationship to drug exposure.

The following adverse reactions have been identified during postapproval use of sevelamer hydrochloride or sevelamer carbonate: hypersensitivity, pruritus, rash, abdominal pain, bleeding gastrointestinal ulcers, colitis, ulceration, necrosis, fecal impaction, and uncommon cases of ileus, intestinal obstruction, and intestinal perforation. Appropriate medical management should be given to patients who develop constipation or have worsening of existing constipation to avoid severe complications.

7 DRUG INTERACTIONS

There are no empirical data on avoiding drug interactions between Renvela and most concomitant oral drugs. For oral medication where a reduction in the bioavailability of that medication would have a clinically significant effect on its safety or efficacy (e.g., cyclosporine, tacrolimus, levothyroxine), consider separation of the timing of the administration of the two drugs [see Clinical Pharmacology (12.3)] . The duration of separation depends upon the absorption characteristics of the medication concomitantly administered, such as the time to reach peak systemic levels and whether the drug is an immediate-release or an extended-release product. Where possible consider monitoring clinical responses and/or blood levels of concomitant drugs that have a narrow therapeutic range.

Table 5: Sevelamer Drug Interactions
Oral drugs for which sevelamer did not alter the pharmacokinetics when administered concomitantly
Digoxin
Enalapril
Iron
Metoprolol
Warfarin
Oral drugs that have demonstrated interaction with sevelamer and are to be dosed separately from Renvela
 | Dosing Recommendations
Ciprofloxacin | Take at least 2 hours before or 6 hours after sevelamer
Mycophenolate mofetil | Take at least 2 hours before sevelamer

8 USE IN SPECIFIC POPULATIONS

8.1 Pregnancy

Risk Summary

Sevelamer carbonate is not absorbed systemically following oral administration and maternal use is not expected to result in fetal exposure to the drug.

Clinical Considerations

Sevelamer carbonate may decrease serum levels of fat-soluble vitamins and folic acid in pregnant women [see Clinical Pharmacology (12.2)] . Consider supplementation.

Data

Animal data

In pregnant rats given dietary doses of 0.5, 1.5, or 4.5 g/kg/day of sevelamer hydrochloride during organogenesis, reduced or irregular ossification of fetal bones, probably due to a reduced absorption of fat-soluble vitamin D, occurred in mid and high-dose groups (human equivalent doses approximately equal to 3–4 times the maximum clinical trial dose of 13 g). In pregnant rabbits given oral doses of 100, 500, or 1000 mg/kg/day of sevelamer hydrochloride by gavage during organogenesis, an increase of early resorptions occurred in the high-dose group (human equivalent dose twice the maximum clinical trial dose).

8.2 Lactation

Risk Summary

Renvela is not absorbed systemically by the mother following oral administration, andbreastfeeding is not expected to result in exposure of the child to Renvela.

Clinical Considerations

Sevelamer carbonate may decrease serum levels of fat-soluble vitamins and folic acid in pregnant women [see Clinical Pharmacology (12.2)] . Consider supplementation.

8.4 Pediatric Use

The safety and efficacy of Renvela in lowering serum phosphorus levels was studied in patients 6 years of age and older with CKD. In this study, Renvela was apparently less effective in children with a low baseline serum phosphorus, which described children <13 years of age and children not on dialysis. Given its mechanism of action, Renvela is expected to be effective in lowering serum phosphorus levels in pediatric patients with CKD. Most adverse events that were reported as related, or possibly related, to sevelamer carbonate were gastrointestinal in nature. No new risks or safety signals were identified with the use of sevelamer carbonate in the trial.

Renvela has not been studied in pediatric patients below 6 years of age.

8.5 Geriatric Use

Clinical studies of Renvela did not include sufficient numbers of subjects aged 65 and over to determine whether they respond differently from younger subjects. Other reported clinical experience has not identified differences in responses between the elderly and younger patients. In general, dose selection for an elderly patient should be cautious, usually starting at the low end of the dosing range.

10 OVERDOSAGE

In CKD patients on dialysis, the maximum dose studied was 14 grams of sevelamer carbonate and 13 grams of sevelamer hydrochloride. There are no reports of overdosage with sevelamer carbonate or sevelamer hydrochloride in patients. Since sevelamer is not absorbed, the risk of systemic toxicity is low.

11 DESCRIPTION

The active ingredient in Renvela is sevelamer carbonate, a polymeric amine that binds phosphate and is meant for oral administration. It was developed as a pharmaceutical alternative to sevelamer hydrochloride (Renagel®). Sevelamer carbonate is an anion exchange resin, with the same polymeric structure as sevelamer hydrochloride, in which carbonate replaces chloride as the counterion. While the counterions differ for the two salts, the polymer itself, the active moiety involved in phosphate binding, is the same.

Renvela (sevelamer carbonate) is known chemically as poly(allylamine- co-N,N′-diallyl-1,3-diamino-2-hydroxypropane) carbonate salt. Sevelamer carbonate is hygroscopic, but insoluble in water. The structure is represented in Figure 1.

Figure 1: Chemical Structure of Sevelamer Carbonate

a, b = number of primary amine groups

a + b = 9

c = number of cross-linking groups

c = 1

m = large number to indicate extended polymer network

Renvela Tablets:Each film-coated tablet of Renvela contains 800 mg of sevelamer carbonate on an anhydrous basis. The inactive ingredients are hypromellose, diacetylated monoglycerides, microcrystalline cellulose, sodium chloride, and zinc stearate.

Renvela Powder:Each packet of Renvela powder contains 0.8 or 2.4 g of sevelamer carbonate on an anhydrous basis. The inactive ingredients are natural and artificial citrus flavor, propylene glycol alginate, sodium chloride, sucralose, and ferric oxide (yellow).

12 CLINICAL PHARMACOLOGY

12.1 Mechanism of Action

Renvela contains sevelamer carbonate, a non-absorbed phosphate-binding cross-linked polymer, free of metal and calcium. It contains multiple amines separated by one carbon from the polymer backbone. These amines exist in a protonated form in the intestine and interact with phosphate molecules through ionic and hydrogen bonding. By binding phosphate in the gastrointestinal tract and decreasing absorption, sevelamer carbonate lowers the phosphate concentration in the serum (serum phosphorus).

12.2 Pharmacodynamics

In addition to effects on serum phosphorus levels, sevelamer hydrochloride has been shown to bind bile acids in vitroand in vivoin experimental animal models. Because sevelamer binds bile acids, it may interfere with normal fat absorption and thus may reduce absorption of fat-soluble vitamins such as A, D and K. In clinical trials of sevelamer hydrochloride, both the mean total and LDL cholesterol declined by 15%–31%; the clinical significance of this finding, which was observed after 2 weeks, is unclear. Triglycerides, HDL cholesterol, and albumin did not change.

12.3 Pharmacokinetics

A mass balance study using^14C-sevelamer hydrochloride, in 16 healthy male and female volunteers showed that sevelamer hydrochloride is not systemically absorbed. No absorption studies have been performed in patients with renal disease.

Drug Interactions

In vivo

Sevelamer carbonate has been studied in human drug-drug interaction studies (9.6 grams once daily with a meal) with warfarin and digoxin. Sevelamer hydrochloride, which contains the same active moiety as sevelamer carbonate, has been studied in human drug-drug interaction studies (2.4–2.8 grams single dose or three times daily with meals or two times daily without meals) with ciprofloxacin, digoxin, enalapril, iron, metoprolol, mycophenolate mofetil, and warfarin.

Coadministered single dose of 2.8 grams of sevelamer hydrochloride in fasted state decreased the bioavailability of ciprofloxacin by approximately 50% in healthy subjects.

Concomitant administration of sevelamer and mycophenolate mofetil in adult and pediatric patients decreased the mean MPA Cmaxand AUC0–12hby 36% and 26%, respectively.

Sevelamer carbonate or sevelamer hydrochloride did not alter the pharmacokinetics of enalapril, digoxin, iron, metoprolol, and warfarin when coadministered.

During postmarketing experience, cases of increased thyroid stimulating hormone (TSH) levels have been reported in patients coadministered sevelamer hydrochloride and levothyroxine. Reduction in concentrations of cyclosporine and tacrolimus leading to dose increases has also been reported in transplant patients when coadministered with sevelamer hydrochloride without any clinical consequences (for example, graft rejection). The possibility of an interaction cannot be excluded with these drugs.

13 NONCLINICAL TOXICOLOGY

13.1 Carcinogenesis, Mutagenesis, Impairment of Fertility

Standard lifetime carcinogenicity bioassays were conducted in mice and rats. Rats were given sevelamer hydrochloride by diet at 0.3, 1, or 3 g/kg/day. There was an increased incidence of urinary bladder transitional cell papilloma in male rats of the high dose group (human equivalent dose twice the maximum clinical trial dose of 13 g). Mice received dietary administration of sevelamer hydrochloride at doses of up to 9 g/kg/day (human equivalent dose 3 times the maximum clinical trial dose). There was no increased incidence of tumors observed in mice.

In an in vitromammalian cytogenetic test with metabolic activation, sevelamer hydrochloride caused a statistically significant increase in the number of structural chromosome aberrations. Sevelamer hydrochloride was not mutagenic in the Ames bacterial mutation assay.

Sevelamer hydrochloride did not impair the fertility of male or female rats in a dietary administration study in which the females were treated from 14 days prior to mating through gestation and the males were treated for 28 days prior to mating. The highest dose in this study was 4.5 g/kg/day (human equivalent dose 3 times the maximum clinical trial dose of 13 g).

14 CLINICAL STUDIES

The ability of sevelamer to control serum phosphorus in CKD patients on dialysis was predominantly determined from the effects of the hydrochloride salt to bind phosphate. Six clinical trials used sevelamer hydrochloride and three clinical trials used sevelamer carbonate. The sevelamer hydrochloride studies include one double-blind, placebo-controlled 2-week study (sevelamer N=24); two open-label, uncontrolled, 8-week studies (sevelamer N=220); and three active-controlled open-label studies with treatment durations of 8 to 52 weeks (sevelamer N=256). The sevelamer carbonate studies include one double-blind, active-controlled, cross-over study with two 8-week treatment periods using sevelamer carbonate tablets (N=79); one open-label, active-controlled, cross-over study with two 4-week treatment periods using sevelamer carbonate powder (N=31); and one randomized, parallel, open-label study using sevelamer carbonate powder (N=144) dosed once daily or sevelamer hydrochloride tablets (N=73) dosed three times daily for 24 weeks. Six of the active-controlled studies are described here (three sevelamer carbonate and three sevelamer hydrochloride studies).

14.1 Cross-Over Study of Sevelamer Carbonate (Renvela) 800 mg Tablets and Sevelamer Hydrochloride (Renagel) 800 mg Tablets

Stage 5 CKD patients on hemodialysis were entered into a five-week sevelamer hydrochloride run-in period and 79 patients received, in random order, sevelamer carbonate 800 mg tablets and sevelamer hydrochloride 800 mg tablets for eight weeks each, with no intervening washout. Study dose during the cross-over period was determined based on the sevelamer hydrochloride dose during the run-in period on a gram-per-gram basis. The phosphorus levels at the end of each of the two cross-over periods were similar. Average actual daily dose was 6 g/day divided among meals for both treatments. Thirty-nine of those completing the cross-over portion of the study were entered into a two-week washout period during which patients were instructed not to take any phosphate binders; this confirmed the activity of sevelamer in this study.

14.2 Cross-Over Study of Sevelamer Carbonate (Renvela) Powder and Sevelamer Hydrochloride (Renagel) Tablets

Stage 5 CKD patients on hemodialysis were entered into a four-week sevelamer hydrochloride run-in period and 31 patients received, in random order, sevelamer carbonate powder and sevelamer hydrochloride tablets for four weeks each with no intervening washout. Study dose during the cross-over period was determined based on the sevelamer hydrochloride dose during the run-in period on a gram-per-gram basis. The phosphorus levels at the end of each of the two cross-over periods were similar. Average actual daily dose was 6.0 g/day divided among meals for sevelamer carbonate powder and 6.4 g/day divided among meals for sevelamer hydrochloride tablets.

14.3 Clinical Study of Sevelamer Carbonate (Renvela) Powder and Tablets in Pediatric Patients

A clinical study with sevelamer carbonate was conducted in 101 patients 6 to 18 years of age with chronic kidney disease. This study included a washout period for patients on a phosphate binder, a 2-week, double-blind, fixed-dose period (FDP) in which patients were randomized to sevelamer carbonate (n=50) or placebo (n=51), and a 26-week, open-label, sevelamer carbonate dose titration period (DTP). Most patients were 13 to 18 years of age (73%) and had a BSA ≥1.2 m^2(84%). Approximately 78% of patients were CKD patients on dialysis.

Sevelamer carbonate significantly reduced serum phosphorus through Week 2 (primary endpoint) by an LS Mean difference of -0.90 (SE 0.27) mg/dL compared to placebo (p=0.001). A similar treatment response was observed in patients who received sevelamer carbonate during the 6-month open-label DTP. Approximately 30% of subjects reached their target serum phosphorus. The median prescribed daily dose was approximately 7.0 g per day during the titration period.

The results of the primary efficacy endpoint were consistent by BSA subgroup. In contrast, a treatment effect was not observed in subjects with a baseline serum phosphorus below 7 mg/dL, many of whom were the subjects 6 to <13 years of age or the subjects not on dialysis (Figure 2).

Figure 2: Change in Serum Phosphorus (mg/dL) from Baseline to Week 2 by Subgroup

[a]: LS Mean difference of Sevelamer Carbonate – Placebo, based on ANCOVA within subgroup and with treatment as fixed effect and screening BSA and baseline serum phosphorus as covariates.

14.4 Sevelamer Hydrochloride versus Active-Control, Cross-Over Study in Hemodialysis Patients

Eighty-four CKD patients on hemodialysis who were hyperphosphatemic (serum phosphorus >6.0 mg/dL) following a two-week phosphate binder washout period were randomized in a cross-over design to receive in random order sevelamer hydrochloride and active control for eight weeks each. Treatment periods were separated by a two-week phosphate binder washout period. Patients started on treatment three times per day with meals. Over each eight-week treatment period, at three separate time points the dose of sevelamer hydrochloride could be titrated up to control serum phosphorus, the dose of active control could also be altered to attain phosphorus control. Both treatments significantly decreased mean serum phosphorus by about 2 mg/dL (Table 6).

Table 6: Mean Serum Phosphorus (mg/dL) at Baseline and Endpoint
 | Sevelamer Hydrochloride (N=81) | Active Control (N=83)
Baseline at End of Washout | 8.4 | 8.0
Endpoint | 6.4 | 5.9
Change from Baseline at Endpoint | -2.0 [p<0.0001, within treatment group comparison] | -2.1
(95% Confidence Interval) | (-2.5, -1.5) | (-2.6, -1.7)

The distribution of responses is shown in Figure 3. The distributions are similar for sevelamer hydrochloride and active control. The median response is a reduction of about 2 mg/dL in both groups. About 50% of subjects have reductions between 1 and 3 mg/dL.

Figure 3: Percentage of Patients (Y-axis) Attaining a Phosphorus Reduction from Baseline (mg/dL) at Least as Great as the Value of the X-axis

Average daily sevelamer hydrochloride dose at the end of treatment was 4.9 g (range of 0.0 to 12.6 g).

14.5 Sevelamer Hydrochloride versus Active Control in Hemodialysis Patients

Two hundred CKD patients on hemodialysis who were hyperphosphatemic (serum phosphorus >5.5 mg/dL) following a two-week phosphate-binder washout period were randomized to receive sevelamer hydrochloride 800 mg tablets (N=99) or an active control (N=101). At week 52, using last observation carried forward, sevelamer and active control both significantly decreased mean serum phosphorus (Table 7).

Table 7: Mean Serum Phosphorus (mg/dL) and Ion Product at Baseline and Change from Baseline to End of Treatment
 | Sevelamer HCl (N=94) | Active Control (N=98)
Phosphorus
Baseline | 7.5 | 7.3
Change from Baseline at Endpoint | -2.1 | -1.8
Ca × Phosphorus Ion Product
Baseline | 70.5 | 68.4
Change from Baseline at Endpoint | -19.4 | -14.2

Sixty-one percent of sevelamer hydrochloride patients and 73% of the control patients completed the full 52 weeks of treatment.

Figure 4, a plot of the phosphorus change from baseline for the completers, illustrates the durability of response for patients who are able to remain on treatment.

Figure 4: Mean Phosphorus Change from Baseline for Patients who Completed 52 Weeks of Treatment

Average daily sevelamer hydrochloride dose at the end of treatment was 6.5 g (range of 0.8 to 13 g).

14.6 Sevelamer Hydrochloride versus Active Control in Peritoneal Dialysis Patients

One hundred and forty-three patients on peritoneal dialysis who were hyperphosphatemic (serum phosphorus >5.5 mg/dL) following a two-week phosphate binder washout period were randomized to receive sevelamer hydrochloride (N=97) or active control (N=46) open label for 12 weeks. Average daily sevelamer hydrochloride dose at the end of treatment was 5.9 g (range 0.8 to 14.3 g). Thirteen patients (14%) in the sevelamer group and 9 patients (20%) in the active-control group discontinued, mostly for gastrointestinal adverse reactions. There were statistically significant changes in serum phosphorus (p<0.001) for sevelamer hydrochloride (-1.6 mg/dL from baseline of 7.5 mg/dL), similar to the active control.

14.7 Once-Daily versus Three-Times-Per-Day Dosing

Stage 5 CKD patients on hemodialysis with a serum phosphate level of >5.5 mg/dL after washout from baseline therapies were randomized in a 2:1 ratio to receive either sevelamer carbonate powder once daily (N=144) or sevelamer hydrochloride as a tablet with the dose divided three times per day (N=73) for 24 weeks. The initial dose for the two groups was 4.8 g/day. At the end of the study, the total daily dose was 6.2 g/day of sevelamer carbonate powder once daily and 6.7 g/day of sevelamer hydrochloride tablets three times per day. A greater percentage of subjects on the once-daily dose than three-times-per-day regimen discontinued therapy prematurely, 35% versus 15%. The reasons for discontinuation were largely driven by adverse events and withdrawal of consent in the once-daily dosing regimen. Serum phosphate levels and calcium-phosphate product were better controlled on the three-times-per-day regimen than on the once-daily regimen. Mean serum phosphorus decreased 2.0 mg/dL for sevelamer carbonate powder once daily and 2.9 mg/dL for sevelamer hydrochloride tablets three times per day.

16 HOW SUPPLIED/STORAGE AND HANDLING

Tablets: Renvela®(sevelamer carbonate) tablets, for oral use is supplied as white oval, film-coated, compressed tablets, engraved with RV800 on one side, containing 800 mg of sevelamer carbonate on an anhydrous basis.

1 Bottle of 270 ct 800 mg tablets (NDC 58468-0133-1)

Powder: Renvela®(sevelamer carbonate) for oral suspension is supplied as opaque, foil-lined, heat-sealed, packets containing 0.8 g or 2.4 g of sevelamer carbonate on an anhydrous basis.

1 Box (NDC 58468-0131-2) of 90 ct 2.4 g packets (NDC 58468-0131-1)

1 Box (NDC 58468-0132-2) of 90 ct 0.8 g packets (NDC 58468-0132-1)

STORAGE AND HANDLING

Storage:Store at 25°C (77°F): excursions permitted to 15°C–30°C (59°F–86°F).

[See USP controlled room temperature]

Protect from moisture.

17 PATIENT COUNSELING INFORMATION

Inform patients to take Renvela with meals and adhere to their prescribed diets.

For patients using an oral medication where a reduction in the bioavailability of that medication would have a clinically significant effect on its safety or efficacy, advise the patient to take the oral medication at least one hour before or three hours after Renvela.

For Renvela powder, brief the patient on preparation of the powder in water.

Advise patients to report new onset or worsening of existing constipation or bloody stools promptly to their physician [see Warnings and Precautions (5.1)] .

Manufactured by:
Sanofi Winthrop Industrie
1 rue de la Vierge
Ambares et Lagrave
33565 Carbon Blanc cedex
France

ROVI Pharma Industrial Services, S.A.
Vía Complutense, 140, Alcalá de Henares,
Madrid, 28805, Spain

For: Genzyme Corporation
Cambridge, MA 02141
A SANOFI COMPANY

Renvela is a registered trademark of Genzyme Corporation.

Package Label - Principal Display Panel - 800 mg Tablets, 270 per Bottle Imprint "RENVELA800"

Package Label - Principal Display Panel - 800 mg Tablets, 270 per Bottle

NDC 58468-0130-1

Rx only

Renvela®

sevelamer carbonate

tablets

800 mg

270 film-Coated Tablets

USUAL DOSAGE:
SEE PACKAGE INSERT
FOR DOSAGE INFORMATION.

Manufactured by:
Genzyme Ireland Ltd.
For: Genzyme Corporation
Cambridge, MA 02142 USA

Package Label - Principal Display Panel - 2.4 g Packets, 90 per Carton

NDC 58468-0131-2

Rx only

Renvela®

sevelamer carbonate

For oral suspension

2.4 g packets

Citrus Flavor

Package Label - Principal Display Panel - 0.8 g Packets, 90 per Carton

NDC 58468-0132-2

Rx only

Renvela®

sevelamer carbonate

For oral suspension

0.8 g packets

Citrus Flavor

Package Label - Principal Display Panel - 800 mg Tablets, 270 per Bottle Imprint "RV800"

Package Label - Principal Display Panel - 800 mg Tablets, 270 per Bottle

NDC 58468-0133-1

Rx only

Renvela®

sevelamer carbonate

tablets

800 mg

270 film-Coated Tablets

USUAL DOSAGE:
SEE PACKAGE INSERT
FOR DOSAGE INFORMATION.

Manufactured by:
Genzyme Ireland Ltd.
For: Genzyme Corporation
Cambridge, MA 02142 USA

PACKAGE LABEL

Package Label - Principal Display Panel - 800 mg Tablets, 30 per Bottle

NDC 58468-0130-2

Rx only

Renvela®

sevelamer carbonate

tablets

800 mg

30 film-Coated Tablets

USUAL DOSAGE:
SEE PACKAGE INSERT
FOR DOSAGE INFORMATION.

Manufactured by:
Genzyme Ireland Ltd.
For: Genzyme Corporation
Cambridge, MA 02142 USA